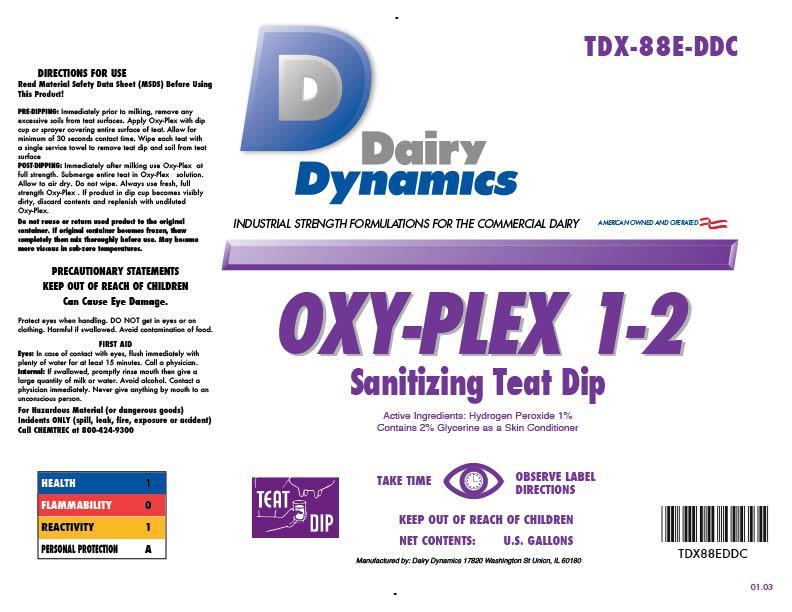 DRUG LABEL: OXY-PLEX 1-2
NDC: 67351-988 | Form: SOLUTION
Manufacturer: Dairy Dynamics L.L.C.
Category: animal | Type: OTC ANIMAL DRUG LABEL
Date: 20150119

ACTIVE INGREDIENTS: HYDROGEN PEROXIDE 2.4 g/1 L
INACTIVE INGREDIENTS: WATER; UREA; GLYCERIN; SODIUM LAURETH-3 SULFATE; LACTIC ACID; SODIUM HYDROXIDE; EDETATE SODIUM; FD&C YELLOW NO. 6

Dairy Dynamics
OXY-PLEX 1-2
Sanitizing Teat Dip

Dairy Dynamics

INDUSTRIAL STRENGTH FORMULATIONS FOR THE COMMCERCIAL DAIRY

AMERICAN OWNED AND OPERATED

DIRECTIONS FOR USE

Read Material Safety Data Sheet (MSDS) Before Using This Product!

PRE-DIPPING: Immediately prior to milking, remove any excessive soils from teat surface. Apply Oxy-Plex with dip cup or sprayer covering entire surface of teat. Allow for minimum of 30 seconds contact time. Wipe each teat with a single service towel to remove teat dip and soil from teat surface.

POST-DIPPING: Immediately after milking use Oxy-Plex at full strength. Submerge entire teat in Oxy-Plex solution. Allow to air dry. Do not wipe. Always use fresh, full strength Oxy-Plex. If product in teat dip cup become visibly dirty, discard contents and replenish with undiluted Oxy-Plex.

Do not reuse or return used product to the original container. If original container becomes frozen, thaw completely then mix thoroughly before use. May become more viscous in sub-zero temperatures.

PRECAUTIONS

PRECAUTIONARY STATEMENTS

KEEP OUT OF REACH OF CHILDREN

Can Cause Eye Damage.

Protect eyes when handling. DO NOT get in eyes or on clothing. Harmful if swallowed. Avoid contamination of food.

FIRST AID

Eyes: in case of contact with eyes, flush immediately with plenty of water for at least 15 minutes. Call a physician.

Internal: if swallowed, promptly rinse mouth then give a large quantity of milk or water. Avoid alcohol. Contact a physician immediately. Never give anything by mouth to an unconscious person.

For Hazardous Materials (or dangerous goods) Incidents ONLY (spill, leak, fire, exposure or accident) Call CHEMTREC at 800-424-9300

HEALTH 1

FLAMMABILITY 0

REACTIVITY 1

PERSONL PROTECTION A

Active Ingredients: Hydrogen Peroxide 1%

Contains 2% Glycerine as a Skin Conditioner

TEAT DIP

TAKE TIME OBSERVE LABEL DIRECTIONS

KEEP OUT OF REACH OF CHILDREN

NET CONTENTS: U.S. GALLONS

Manufactured by: Dairy Dynamics 17820 Washington St Union, IL 60180

TDX-87E-DDC

TDX87EDDC

01.03